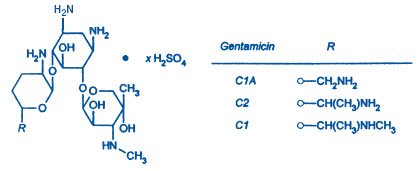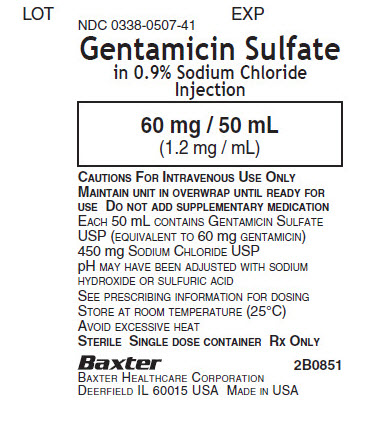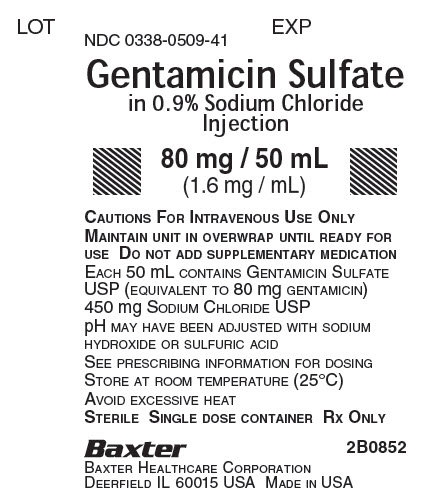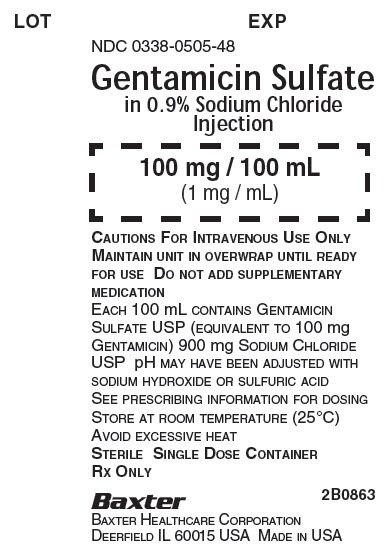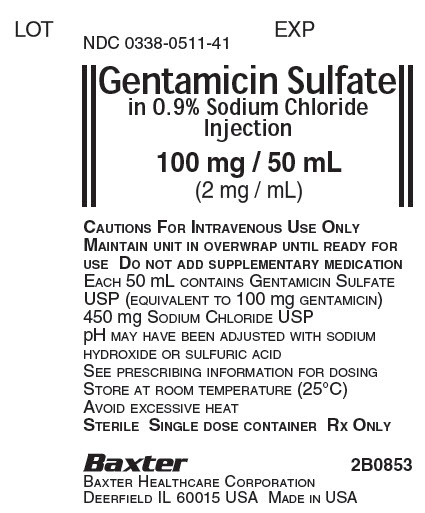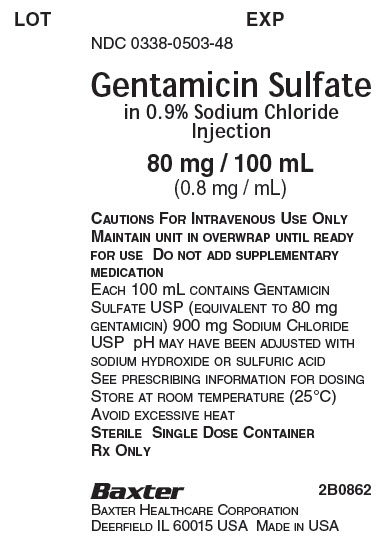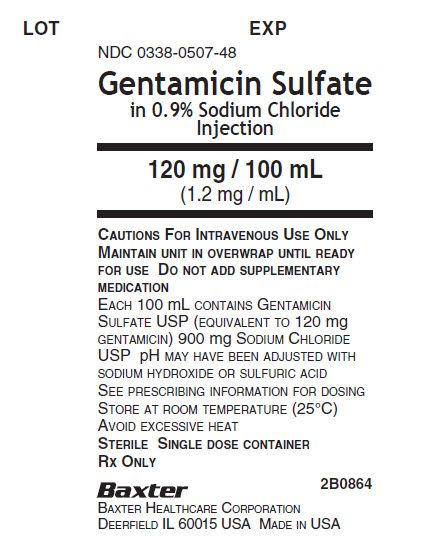 DRUG LABEL: Gentamicin Sulfate in Sodium Chloride
NDC: 0338-0507 | Form: INJECTION, SOLUTION
Manufacturer: Baxter Healthcare Corporation
Category: prescription | Type: HUMAN PRESCRIPTION DRUG LABEL
Date: 20230126

ACTIVE INGREDIENTS: GENTAMICIN SULFATE 60 mg/50 mL
INACTIVE INGREDIENTS: SODIUM HYDROXIDE; SULFURIC ACID; WATER; SODIUM CHLORIDE 450 mg/50 mL

Gentamicin Sulfate in 0.9% Sodium Chloride Injection
in Plastic Container
VIAFLEX PLUS Container
For Intravenous Administration
Further Dilution Not Required

Rx Only

To reduce the development of drug-resistant bacteria and maintain the effectiveness of Gentamicin Sulfate in 0.9% Sodium Chloride Injection and other antibacterial drugs, Gentamicin Sulfate in 0.9% Sodium Chloride Injection should be used only to treat or prevent infections that are proven or strongly suspected to be caused by bacteria.

WARNINGS

Patients treated with aminoglycosides should be under close clinical observation because of the potential toxicity associated with their use.

As with other aminoglycosides, gentamicin sulfate is potentially nephrotoxic. The risk of nephrotoxicity is greater in patients with impaired renal function and in those who receive high dosage or prolonged therapy.

Neurotoxicity manifested by ototoxicity, both vestibular and auditory, can occur in patients treated with gentamicin sulfate, primarily those with pre-existing renal damage and in patients with normal renal function treated with higher doses and/or for longer periods than recommended. Aminoglycoside-induced ototoxicity is usually irreversible. Other manifestations of neurotoxicity may include numbness, skin tingling, muscle twitching and convulsions.

Renal and eighth cranial nerve function should be closely monitored, especially in patients with known or suspected reduced renal function at onset of therapy and also in those whose renal function is initially normal but who develop signs of renal dysfunction during therapy. Urine should be examined for decreased specific gravity, increased excretion of protein, and the presence of cells or casts. Blood urea nitrogen (BUN), serum creatinine, or creatinine clearance should be determined periodically. When feasible, it is recommended that serial audiograms be obtained in patients old enough to be tested, particularly high-risk patients. Evidence of ototoxicity (dizziness, vertigo, tinnitus, roaring in the ears or hearing loss) or nephrotoxicity requires dosage adjustment or discontinuance of the drug. As with the other aminoglycosides, on rare occasions changes in renal and eighth cranial nerve function may not become manifest until soon after completion of therapy.

Serum concentrations of aminoglycosides should be monitored when feasible to assure adequate levels and to avoid potentially toxic levels. When monitoring gentamicin peak concentrations, dosage should be adjusted so that prolonged levels above 12 mcg/mL are avoided. When monitoring gentamicin trough concentrations, dosage should be adjusted so that levels above 2 mcg/mL are avoided. Excessive peak and/or trough serum concentrations of aminoglycosides may increase the risk of renal and eighth cranial nerve toxicity. In the event of overdose or toxic reactions, hemodialysis may aid in the removal of gentamicin from the blood, especially if renal function is, or becomes compromised. The rate of removal of gentamicin is considerably lower by peritoneal dialysis than it is by hemodialysis.

Concurrent and/or sequential systemic or topical use of other potentially neurotoxic and/or nephrotoxic drugs, such as cisplatin, cephaloridine, kanamycin, amikacin, neomycin, polymyxin B, colistin, paromomycin, streptomycin, tobramycin, vancomycin, and viomycin, should be avoided (see PRECAUTIONS, Drug Interactions section).

Other factors which may increase patient risk of toxicity are advanced age and dehydration (see PRECAUTIONS, Geriatric Use and DOSAGE AND ADMINISTRATION sections).

The concurrent use of gentamicin with potent diuretics, such as ethacrynic acid or furosemide, should be avoided, since certain diuretics by themselves may cause ototoxicity. In addition, when administered intravenously, diuretics may enhance aminoglycoside toxicity by altering the antibiotic concentration in serum and tissue (see PRECAUTIONS, Drug Interactions section).

Aminoglycosides can cause fetal harm when administered to a pregnant woman (see WARNINGS and PRECAUTIONS, Pregnancy sections).

DESCRIPTION

Gentamicin Sulfate, USP, a water soluble antibiotic of the aminoglycoside group, is derived from Micromonospora purpurea, and actinomycete.

Gentamicin Sulfate in 0.9% Sodium Chloride Injection is a sterile, nonpyrogenic solution of Gentamicin Sulfate, USP in water for injection with 9 mg/mL sodium chloride (NaCl) to provide isotonicity. The solution is intended for intravenous use and requires no further dilution. pH may be adjusted with sulfuric acid or sodium hydroxide and is approximately 4.5.

This VIAFLEX PLUS plastic container is fabricated from a specially formulated polyvinyl chloride (PL 146 Plastic). VIAFLEX PLUS on the container indicates the presence of a drug additive in a drug vehicle. The VIAFLEX PLUS plastic container system utilizes the same container as the VIAFLEX plastic container system. The amount of water that can permeate from inside the container into the overwrap is insufficient to affect the solution significantly. Solutions in contact with the plastic container can leach out certain of its chemical components in very small amounts within the expiration period, e.g., di-2-ethylhexyl phthalate (DEHP), up to 5 parts per million. However, the safety of the plastic has been confirmed in tests in animals according to USP biological tests for plastic containers as well as by tissue culture toxicity studies.

CLINICAL PHARMACOLOGY

After intramuscular (IM) administration of gentamicin sulfate, peak serum concentrations usually occur between 30 to 60 minutes and serum levels are measurable for 6 to 8 hours. When gentamicin is administered by intravenous (IV) infusion over a two-hour period, the serum concentrations are similar to those obtained by intramuscular administration.

In patients with normal renal function, peak serum concentrations of gentamicin (mcg/mL) are usually up to four times the single intramuscular dose (mg/kg); for example, a 1 mg/kg injection in adults may be expected to result in a peak serum concentration up to 4 mcg/mL; a 1.5 mg/kg dose may produce levels up to 6 mcg/mL. While some variation is to be expected due to a number of variables such as age, body temperature, surface area and physiologic differences, the individual patient given the same dose tends to have similar levels in repeated determinations. Gentamicin administered at 1 mg/kg every eight hours for the usual 7- to 10-day treatment period to patients with normal renal function does not accumulate in the serum.

Gentamicin, like all aminoglycosides, may accumulate in the serum and tissue of patients treated with higher doses and/or for prolonged periods, particularly in the presence of impaired renal function. In adult patients, treatment with gentamicin dosages of 4 mg/kg/day or higher for seven to ten days may result in a slight, progressive rise in both peak and trough concentrations. In patients with impaired renal function, gentamicin is cleared from the body more slowly than in patients with normal renal function. The more severe the impairment, the slower the clearance. Dosage must be adjusted.

Since gentamicin is distributed in extracellular fluid, peak serum concentrations may be lower than usual in adult patients who have a large volume of this fluid. Serum concentrations of gentamicin in febrile patients may be lower than those in afebrile patients given the same dose. When body temperature returns to normal, serum concentrations of the drug may rise. Febrile and anemic states may be associated with a shorter than usual serum half-life. (Dosage adjustment is usually not necessary.) In severely burned patients, the half-life may be significantly decreased and resulting serum concentrations may be lower than anticipated from the mg/kg dose.

Protein binding studies have indicated that the degree of gentamicin binding is low. Depending upon the methods used for testing, this may be between 0 and 30%.

After initial administration to patients with normal renal function, generally 70% or more of the gentamicin dose is recoverable in the urine in 24 hours; concentrations in urine above 100 mcg/mL may be achieved. Little, if any, metabolic transformation occurs; the drug is excreted principally by glomerular filtration. After several days of treatment, the amount of gentamicin excreted in the urine approaches the daily dose administered. As with other aminoglycosides, a small amount of the gentamicin dose may be retained in the tissues, especially in the kidneys. Minute quantities of aminoglycosides have been detected in the urine weeks after the drug administration was discontinued. Renal clearance of gentamicin is similar to that of endogenous creatinine.

In patients with marked impairment of renal function, there is a decrease in the concentration of aminoglycosides in urine and in their penetration into defective renal parenchyma. This decreased drug excretion, together with the potential nephrotoxicity of aminoglycosides, should be considered when treating such patients who have urinary tract infections.

Probenecid does not affect renal tubular transport of gentamicin.

The endogenous creatinine clearance rate and serum creatinine level have a high correlation with the half-life of gentamicin in serum. Results of these tests may serve as guides for adjusting dosage in patients with renal impairment (see DOSAGE AND ADMINISTRATION).

Following parenteral administration, gentamicin can be detected in serum, lymph, tissues, sputum, and in pleural, synovial, and peritoneal fluids. Concentrations in renal cortex sometimes may be eight times higher than the usual serum levels. Concentrations in bile, in general, have been low and have suggested minimal biliary excretion. Gentamicin crosses the peritoneal as well as the placental membranes (see PRECAUTIONS, Pregnancy section). Since aminoglycosides diffuse poorly into the subarachnoid space after parenteral administration, concentrations of gentamicin in cerebrospinal fluid are often low and dependent upon dose, rate of penetration, and degree of meningeal inflammation. There is minimal penetration of gentamicin into ocular tissues following intramuscular or intravenous administration.

Microbiology

Mechanism of Action

Gentamicin, an aminoglycoside, binds to the prokaryotic ribosome, inhibiting protein synthesis in susceptible bacteria. It is bactericidal in vitro against Gram-positive and Gram-negative bacteria.

Mechanism of Resistance

Bacterial resistance to gentamicin is generally developed slowly. Bacteria resistant to one aminoglycoside may be resistant to one or more other aminoglycosides. The following bacteria are usually resistant to the aminoglycosides, including gentamicin: most streptococcal species (including Streptococcus pneumoniae and the Group D streptococci), most enterococcal species (including Enterococcus faecalis, E. faecium, and E. durans), and anaerobic organisms, such as Bacteroides species and Clostridium species.

Aminoglycosides are known to be not effective against Salmonella and Shigella species in patients. Therefore, in vitro susceptibility test results should not be reported.

Interactions with Other Antimicrobials

In vitro studies show that an aminoglycoside combined with an antibiotic that interferes with cell wall synthesis may act synergistically against some enterococcal strains. The combination of gentamicin and penicillin G has a synergistic bactericidal effect against strains of Enterococcus faecalis, E. faecium and E. durans. An enhanced killing effect against many of these strains has also been shown in vitro with combinations of gentamicin and ampicillin, carbenicillin, nafcillin or oxacillin.

The combined effect of gentamicin and carbenicillin is synergistic for many strains of Pseudomonas aeruginosa. In vitro synergism against other Gram-negative organisms has been shown with combinations of gentamicin and cephalosporins.

Gentamicin may be active against clinical isolates of bacteria resistant to other aminoglycosides.

Antibacterial Activity

Gentamicin has been shown to be active against most of the following bacteria, both in vitro and in clinical infections [see INDICATIONS AND USAGE].

Gram-Positive Bacteria

Staphylococcus species

Gram-Negative Bacteria

Citrobacter species
Enterobacter species
Escherichia coli
Klebsiella species
Proteus species
Serratia species
Pseudomonas aeruginosa

Susceptibility Test Methods

For specific information regarding susceptibility test interpretive criteria and associated test methods and quality control standards recognized by FDA for this drug, please see: http://www.fda.gov/STIC.

INDICATIONS AND USAGE

To reduce the development of drug-resistant bacteria and maintain the effectiveness of Gentamicin Sulfate in 0.9% Sodium Chloride Injection and other antibacterial drugs, Gentamicin Sulfate in 0.9% Sodium Chloride Injection should be used only to treat or prevent infections that are proven or strongly suspected to be caused by susceptible bacteria. When culture and susceptibility information are available, they should be considered in selecting or modifying antibacterial therapy. In the absence of such data, local epidemiology and susceptibility patterns may contribute to the empiric selection of therapy.

Gentamicin Sulfate in 0.9% Sodium Chloride Injection is indicated in the treatment of serious infections caused by susceptible strains of the following microorganisms: Pseudomonas aeruginosa, Proteus species (indole-positive and indole-negative), Escherichia coli, Klebsiella-Enterobacter- Serratia species, Citrobacter species, and Staphylococcus species (coagulase-positive and coagulase-negative).

Clinical studies have shown gentamicin sulfate to be effective in bacterial neonatal sepsis; bacterial septicemia; and serious bacterial infections of the central nervous system (meningitis), urinary tract, respiratory tract, gastrointestinal tract (including peritonitis), skin, bone and soft tissue (including burns). Aminoglycosides, including gentamicin, are not indicated in uncomplicated initial episodes of urinary tract infections unless the causative organisms are susceptible to these antibiotics and are not susceptible to antibiotics having less potential for toxicity.

Specimens for bacterial culture should be obtained to isolate and identify causative organisms and to determine their susceptibility to gentamicin.

Gentamicin Sulfate in 0.9% Sodium Chloride Injection may be considered as initial therapy in suspected or confirmed gram-negative infections, and therapy may be instituted before obtaining results of susceptibility testing. The decision to continue therapy with this drug should be based on the results of susceptibility tests, the severity of the infection, and the important additional concepts contained in the boxed WARNINGS. If the causative organisms are resistant to gentamicin, other appropriate therapy should be instituted.

In serious infections when the causative organisms are unknown, Gentamicin Sulfate in 0.9% Sodium Chloride Injection may be administered as initial therapy in conjunction with a penicillin-type or cephalosporin-type drug before obtaining results of susceptibility testing. If anaerobic organisms are suspected as etiologic agents, consideration should be given to using other suitable antimicrobial therapy in conjunction with gentamicin. Following identification of the organism and its susceptibility, appropriate antibiotic therapy should then be continued.

Gentamicin injection has been used effectively in combination with carbenicillin for the treatment of life-threatening infections caused by Pseudomonas aeruginosa. It has also been found effective when used in conjunction with a penicillin-type drug for the treatment of endocarditis caused by group D streptococci.

Gentamicin injection has also been shown to be effective in the treatment of serious staphylococcal infections. While not the antibiotic of first choice, gentamicin may be considered when penicillins or other less potentially toxic drugs are contraindicated and bacterial susceptibility tests and clinical judgement indicate its use. It may also be considered in mixed infections caused by susceptible strains of staphylococci and gram-negative organisms.

In the neonate with suspected bacterial sepsis or staphylococcal pneumonia, a penicillin-type drug is also usually indicated as concomitant therapy with gentamicin (see PRECAUTIONS, Pediatric Use and DOSAGE AND ADMINISTRATION sections).

CONTRAINDICATIONS

Hypersensitivity to gentamicin is a contraindication to its use. A history of hypersensitivity or serious toxic reactions to other aminoglycosides may contraindicate use of gentamicin because of known cross-sensitivity of patients to drugs in this class.

WARNINGS

(See boxed WARNINGS.)

Aminoglycosides can cause fetal harm when administered to a pregnant woman. Aminoglycoside antibiotics cross the placenta, and there have been several reports of total irreversible bilateral congenital deafness in children whose mothers received streptomycin during pregnancy. Serious side effects to mother, fetus or newborn have not been reported in the treatment of pregnant women with other aminoglycosides. Animal reproduction studies conducted on rats and rabbits did not reveal evidence of impaired fertility or harm to the fetus due to gentamicin sulfate. It is not known whether gentamicin sulfate can cause fetal harm when administered to a pregnant woman or can affect reproduction capacity. If gentamicin is used during pregnancy or if the patient becomes pregnant while taking gentamicin, she should be apprised of the potential hazard to the fetus.

Solutions containing sodium ions should be used with great care, if at all, in patients with congestive heart failure, severe renal insufficiency, and in clinical states in which there exists edema with sodium retention.

Risk of Ototoxicity Due to Mitochondrial DNA Variants

Cases of ototoxicity with aminoglycosides have been observed in patients with certain variants in the mitochondrially encoded 12S rRNA gene (MT-RNR1), particularly the m.1555A>G variant. Ototoxicity occurred in some patients even when their aminoglycoside serum levels were within the recommended range. Mitochondrial DNA variants are present in less than 1% of the general US population, and the proportion of the variant carriers who may develop ototoxicity as well as the severity of ototoxicity is unknown. In case of known maternal history of ototoxicity due to aminoglycoside use or a known mitochondrial DNA variant in the patient, consider alternative treatments other than aminoglycosides unless the increased risk of permanent hearing loss is outweighed by the severity of infection and lack of safe and effective alternative therapies.

PRECAUTIONS

General

Prescribing Gentamicin Sulfate in 0.9% Sodium Chloride Injection in the absence of a proven or strongly suspected bacterial infection or a prophylactic indication is unlikely to provide benefit to the patient and increases the risk of the development of drug-resistant bacteria.

Do not use additives or premix with other drugs. See DOSAGE AND ADMINISTRATION.

Neurotoxic and nephrotoxic antibiotics may be almost completely absorbed from body surfaces (except the urinary bladder) after local irrigation and after topical application during surgical procedures. The potential toxic effects of antibiotics administered in this fashion (neuromuscular blockade, respiratory paralysis, oto- and nephrotoxicity) should be considered (see boxed WARNINGS).

Aminoglycosides should be used with caution in patients with neuromuscular disorders such as myasthenia gravis or parkinsonism, since these drugs may aggravate muscle weakness because of their potential curare-like effects on the neuromuscular junction. During or following gentamicin therapy, paresthesias, tetany, positive Chvostek and Trousseau signs and mental confusion have been described in patients with hypomagnesemia, hypocalcemia and hypokalemia. When this has occurred in infants, tetany and muscle weakness has been described. Both adults and infants required appropriate corrective electrolyte therapy (see PRECAUTIONS, Pediatric Use section).

A Fanconi-like syndrome, with aminoaciduria and metabolic acidosis has been reported in some adults and infants being given gentamicin injections.

Cross allergenicity among aminoglycosides has been demonstrated.

Patients should be well hydrated during treatment.

Treatment with gentamicin may result in overgrowth of nonsusceptible organisms. If this occurs, appropriate therapy is indicated.

See boxed WARNINGS regarding concurrent use of potent diuretics and regarding concurrent and/or sequential use of other neurotoxic and/or nephrotoxic antibiotics, and for other essential information (see also PRECAUTIONS, Drug Interactions section).

Information for Patients

Patients should be counseled that antibacterial drugs including Gentamicin Sulfate in 0.9% Sodium Chloride Injection should only be used to treat bacterial infections. They do not treat viral infections (e.g., the common cold). When Gentamicin Sulfate in 0.9% Sodium Chloride Injection is prescribed to treat a bacterial infection, patients should be told that although it is common to feel better early in the course of therapy, the medication should be taken exactly as directed. Skipping doses or not completing the full course of therapy may (1) decrease the effectiveness of the immediate treatment and (2) increase the likelihood that bacteria will develop resistance and will not be treatable by Gentamicin Sulfate in 0.9% Sodium Chloride Injection or other antibacterial drugs in the future.

Laboratory Tests

Laboratory abnormalities possibly related to gentamicin include: increased levels of serum transaminase (SGOT, SGPT), serum LDH and billirubin; decreased serum calcium, magnesium, sodium and potassium; anemia, leukopenia, granulocytopenia, transient agranulocytosis, eosinophilia, increased and decreased reticulocyte counts and thrombocytopenia. While clinical laboratory test abnormalities may be isolated findings, they may also be associated with clinically related signs and symptoms. For example, tetany and muscle weakness may be associated with hypomagnesemia, hypocalcemia, and hypokalemia.

Drug Interactions

The concurrent use of gentamicin with potent diuretics, such as ethacrynic acid or furosemide, should be avoided, since certain diuretics by themselves may cause ototoxicity. In addition, when administered intravenously, diuretics may enhance aminoglycoside toxicity by altering the antibiotic concentration in serum and tissue.

Concurrent and/or sequential systemic or topical use of other potentially neurotoxic and/or nephrotoxic drugs such as cisplatin, cephaloridine, kanamycin, amikacin, neomycin, polymyxin B, colistin, paromomycin, streptomycin, tobramycin, vancomycin, and viomycin, should be avoided.

Increased nephrotoxicity has been reported following concomitant administration of aminoglycoside antibiotics and cephalosporins.

Neuromuscular blockade and respiratory paralysis have been reported in the cat receiving high doses (40 mg/kg) of gentamicin. The possibility of these phenomena occurring in man should be considered if aminoglycosides are administered by any route to patients receiving anesthetics, or to patients receiving neuro-muscular blocking agents, such as succinylcholine, tubocurarine, or decamethonium, or in patients receiving massive transfusions of citrate-anticoagulated blood. If neuromuscular blockade occurs, calcium salts may reverse it.

Although the in vitro mixing of gentamicin and carbenicillin results in a rapid and significant inactivation of gentamicin, this interaction has not been demonstrated in patients with normal renal function who received both drugs by different routes of administration. A reduction in gentamicin serum half-life has been reported in patients with severe renal impairment receiving carbenicillin concomitantly with gentamicin.

Probenecid does not affect renal tubular transport of gentamicin.

Pregnancy

See WARNINGS section.

Aminoglycosides can cause fetal harm when administered to a pregnant woman. Aminoglycoside antibiotics cross the placenta and there have been several reports of total irreversible bilateral congenital deafness in children whose mothers received streptomycin during pregnancy. Serious side effects to mother, fetus, or newborn have not been reported in the treatment of pregnant women with other aminoglycosides. Animal reproduction studies conducted on rats and rabbits did not reveal evidence of impaired fertility or harm to the fetus due to gentamicin sulfate. It is not known whether gentamicin sulfate can cause fetal harm when administered to a pregnant woman or can affect reproduction capacity. If gentamicin is used during pregnancy or if the patient becomes pregnant while taking gentamicin, she should be apprised of the potential hazard to the fetus.

Nursing Mothers

It is not known whether this drug is excreted in human milk. Because many drugs are excreted in human milk and because of the potential for serious adverse reactions in nursing infants from gentamicin, a decision should be made whether to discontinue the drug, taking into account the importance of the drug to the mother.

Pediatric Use

In the neonate with suspected bacterial sepsis or staphylococcal pneumonia, a penicillin-type drug is also usually indicated as concomitant therapy with gentamicin.

During or following gentamicin therapy, paresthesias, tetany, positive Chvostek and Trousseau signs and mental confusion have been described in patients with hypomagnesemia, hypocalcemia and hypokalemia. When this has occurred in infants, tetany and muscle weakness have been described. Both adults and infants required appropriate corrective electrolyte therapy.

A Fanconi-like syndrome, with aminoaciduria and metabolic acidosis has been reported in some adults and infants being given gentamicin injections.

Geriatric Use

This drug is known to be substantially excreted by the kidney, and the risk of toxic reactions to this drug may be greater in patients with impaired renal function. Because elderly patients are more likely to have decreased renal function, care should be taken in dose selection, and it may be useful to monitor renal function.

Elderly patients may have reduced renal function which may not be evident in the results of routine screening tests such as BUN or serum creatinine. A creatinine clearance determination may be more useful. Monitoring of renal function during treatment with gentamicin, as with other aminoglycosides, is particularly important in such patients.

ADVERSE REACTIONS

Nephrotoxicity - Adverse renal effects, as demonstrated by the presence of casts, cells, or protein in the urine or by rising BUN, NPN, serum creatinine and oliguria, have been reported. They occur more frequently in patients with a history of renal impairment and in patients treated for longer periods or with larger dosages than recommended.

Neurotoxicity - Serious adverse effects on both vestibular and auditory branches of the eighth cranial nerve have been reported, primarily in patients with renal impairment (especially if hemodialysis is required) and in patients on high doses and/or prolonged therapy. Symptoms include dizziness, vertigo, tinnitus, roaring in the ears and also hearing loss, which, as with the other aminoglycosides, may be irreversible. Hearing loss is usually manifested initially by diminishing high-tone acuity. Other factors which may increase the risk of toxicity include excessive dosage, dehydration and previous exposure to other ototoxic drugs.

Peripheral neuropathy or encephalopathy, including numbness, skin tingling, muscle twitching, convulsions, and a myasthenia gravis-like syndrome, have been reported.

Note: This risk of toxic reactions is low in patients with normal renal function who do not receive gentamicin sulfate at higher doses or for longer periods of time than recommended.

Other reported adverse reactions possibly related to gentamicin include: respiratory depression, lethargy, confusion, depression, visual disturbances, decreased appetite, weight loss, hypotension and hypertension; rash, itching, urticaria, generalized burning, laryngeal edema, anaphylactoid reactions, fever, and headache; nausea, vomiting, increased salivation, and stomatitis; purpura, pseudotumor cerebri, acute organic brain syndrome, pulmonary fibrosis, alopecia, joint pain, transient hepatomegaly, and splenomegaly.

Laboratory abnormalities possibly related to gentamicin include: increased levels of serum transaminase (SGOT, SGPT), serum LDH and bilirubin; decreased serum calcium, magnesium, sodium and potassium; anemia, leukopenia, granulocytopenia, transient agranulocytosis, eosinophilia, increased and decreased reticulocyte counts and thrombocytopenia. While clinical laboratory test abnormalities may be isolated findings, they may also be associated with clinically related signs and symptoms. For example, tetany and muscle weakness may be associated with hypomagnesemia, hypocalcemia, and hypokalemia.

While local tolerance of gentamicin sulfate is generally excellent, there has been an occasional report of pain at the injection site. Subcutaneous atrophy or fat necrosis suggesting local irritation has been reported rarely.

Reactions which may occur because of the solution or the technique of administration include febrile response, infection at the site of injection, venous thrombosis or phlebitis extending from the site of injection, extravasation, and hypervolemia.

If an adverse reaction does occur, discontinue the infusion, evaluate the patient, institute appropriate therapeutic countermeasures, and save the remainder of the fluid for examination if deemed necessary.

OVERDOSAGE

In the event of overdosage or toxic reactions, hemodialysis may aid in the removal of gentamicin from the blood, and is especially important if renal function is, or becomes compromised. The rate of removal of gentamicin is considerably lower by peritoneal dialysis than it is by hemodialysis.

DOSAGE AND ADMINISTRATION

Gentamicin Sulfate in 0.9% Sodium Chloride Injection is for intravenous use only.

The patient’s pretreatment body weight should be obtained for calculation of correct dosage. The dosage of aminoglycosides in obese patients should be based on an estimate of the lean body mass. It is desirable to limit the duration of treatment with aminoglycosides to short term.

Patients with Normal Renal Function

Adults: The recommended dosage of Gentamicin Sulfate in 0.9% Sodium Chloride Injection for patients with serious infections and normal renal function is 3 mg/kg/day administered in three equal doses every eight hours (Table 3).

For patients with life-threatening infections, dosages up to 5 mg/kg/day may be administered in three or four equal doses. The dosage should be reduced to 3 mg/kg/day as soon as clinically indicated (Table 3).

It is desirable to measure both peak and trough serum concentrations of gentamicin to determine the adequacy and safety of the dosage. When such measurements are feasible, they should be carried out periodically during therapy to assure adequate but not excessive drug levels. For example, the peak concentration (at 30 to 60 minutes following cessation of infusion) is expected to be in the range of 4 to 6 mcg/mL. When monitoring peak concentrations, dosage should be adjusted so that prolonged levels above 12 mcg/mL are avoided. When monitoring trough concentrations (just prior to the next dose), dosage should be adjusted so that levels above 2 mcg/mL are avoided. Determination of the adequacy of a serum level for a particular patient must take into consideration the susceptibility of the causative organism, the severity of the infection, and the status of the patient’s host-defense mechanisms.

In patients with extensive burns, altered pharmacokinetics may result in reduced serum concentrations of aminoglycosides. In such patients treated with gentamicin, measurement of serum concentrations is recommended as a basis for dosage adjustment.

Table 3: Dosage Schedule Guide for Adults With Normal Renal Function (Dosage at Eight-Hour Intervals)
Patient’s Weight [The dosage of aminoglycosides in obese patients should be based on an estimate of the lean body mass.] |  | Usual Dose for Serious Infections 1 mg/kg q8h (3 mg/kg/day) | Dose for Life-Threatening Infections (Reduce as Soon as Clinically Indicated) 1.7 mg/kg q8h [For q6h schedules, dosage should be recalculated.] (5 mg/kg/day)
kg | (lb)
 |  | mg/dose q8h | mg/dose q8h
40 | (88) | 40 | 66
45 | (99) | 45 | 75
50 | (110) | 50 | 83
55 | (121) | 55 | 91
60 | (132) | 60 | 100
65 | (143) | 65 | 108
70 | (154) | 70 | 116
75 | (165) | 75 | 125
80 | (176) | 80 | 133
85 | (187) | 85 | 141
90 | (198) | 90 | 150
95 | (209) | 95 | 158
100 | (220) | 100 | 166

Children: 6 to 7.5 mg/kg/day (2 to 2.5 mg/kg administered every eight hours).

Infants and Neonates: 7.5 mg/kg/day (2.5 mg/kg administered every eight hours).

Premature or Full-Term Neonates One Week of Age or Less: 5 mg/kg/day (2.5 mg/kg administered every 12 hours).

NOTE: For further information concerning the use of gentamicin in infants and children, see Pediatric Gentamicin Sulfate Injection product information.

The usual duration of treatment for all patients is seven to ten days. In difficult and complicated infections, a longer course of therapy may be necessary. In such cases monitoring of renal, auditory, and vestibular functions is recommended, since toxicity is more apt to occur with treatment extended for more than ten days. Dosage should be reduced if clinically indicated.

For Intravenous Administration

The intravenous administration of gentamicin may be particularly useful for treating patients with bacterial septicemia or those in shock. It may also be the preferred route of administration for some patients with congestive heart failure, hematologic disorders, severe burns, or those with reduced muscle mass. For intermittent intravenous administration in adults, a single dose of Gentamicin Sulfate in 0.9% Sodium Chloride Injection may be administered according to individual patient requirements from the appropriate premixed container. The solution may be infused over a period of one-half to two hours.

Gentamicin Sulfate Injection should not be physically premixed with other drugs, but should be administered separately in accordance with the recommended route of administration and dosage schedule.

Patients with Impaired Renal Function

Dosage must be adjusted in patients with impaired renal function to assure therapeutically adequate, but not excessive blood levels. Whenever possible, serum concentrations of gentamicin should be monitored. One method of dosage adjustment is to increase the interval between administration of the usual doses. Since the serum creatinine concentration has a high correlation with the serum half-life of gentamicin, this laboratory test may provide guidance for adjustment of the interval between doses. The interval between doses (in hours) may be approximated by multiplying the serum creatinine level (mg/100 mL) by 8. For example, a patient weighing 60 kg with a serum creatinine level of 2 mg/100 mL could be given 60 mg (1 mg/kg) every 16 hours (2 x 8).

In patients with serious systemic infections and renal impairment, it may be desirable to administer the antibiotic more frequently but in reduced dosage. In such patients, serum concentrations of gentamicin should be measured so that adequate, but not excessive levels result. A peak and trough concentration measured intermittently during therapy will provide optimal guidance for adjusting dosage. After the usual initial dose, a rough guide for determining reduced dosage at eight-hour intervals is to divide the normally recommended dose by the serum creatinine level (Table 4). For example, after an initial dose of 60 mg (1 mg/kg), a patient weighing 60 kg with a serum creatinine level of 2 mg/100 mL could be given 30 mg every eight hours (60 ÷ 2). It should be noted that the status of renal function may be changing over the course of the infectious process.

It is important to recognize that deteriorating renal function may require a greater reduction of dosage than that specified in the above guidelines for patients with stable renal impairment.

This container system may be inappropriate for the dosage requirements of children, infants, and neonates. Other dosage forms may be more appropriate.

Table 4: Dosage Adjustment Guide For Patients With Renal Impairment (Dosage at Eight-Hour Intervals After the Usual Initial Dose)
Serum Creatinine (mg %) | Approximate Creatinine Clearance (mL/min/1.73 m^2 | Percent of Usual Doses Shown in Table 3
≤1 | >100 | 100
1.1 - 1.3 | 70 - 100 | 80
1.4 - 1.6 | 55 - 70 | 65
1.7 - 1.9 | 45 - 55 | 55
2 - 2.2 | 40 - 45 | 50
2.3 - 2.5 | 35 - 40 | 40
2.6 - 3 | 30 - 35 | 35
3.1 - 3.5 | 25 - 30 | 30
3.6 - 4 | 20 - 25 | 25
4.1 - 5.1 | 15 - 20 | 20
5.2 - 6.6 | 10 - 15 | 15
6.7 - 8 | <10 | 10

In adults with renal failure undergoing hemodialysis, the amount of gentamicin removed from the blood may vary depending upon several factors including the dialysis method used. An eight hour hemodialysis may reduce serum concentrations of gentamicin by approximately 50%. The recommended dosage at the end of each dialysis period is 1 to 1.7 mg/kg depending upon the severity of infection.

In children, a dose of 2 mg/kg may be administered.

The above dosage schedules are not intended as rigid recommendations but are provided as guides to dosage when the measurement of gentamicin serum levels is not feasible.

A variety of methods are available to measure gentamicin concentrations in body fluids; these include microbiologic, enzymatic and radioimmunoassay techniques.

Gentamicin Sulfate in 0.9% Sodium Chloride Injection is a ready-to-use isotonic solution. No dilution or buffering is required.

If the prescribed dose is exactly 60, 80, or 100 mg use the appropriate container. If the prescribed dose is higher or lower than that of the supplied container adjustments can be made. If the dose is higher than the contents of a 100 mg container the additional amount should be removed from a container of gentamicin sulfate (60 mg/mL) and added to the 100 mg container. If the prescribed dose is less than that contained in a supplied container, use the container with the dose closest to (but above) the prescribed dose, removing and discarding an appropriate amount from it.

Do not use plastic containers in series connection.

Parenteral drug products should be inspected visually for particulate matter and discoloration prior to administration, whenever solution and container permit. Use only if solution is clear and container and seals are intact.

If administration is controlled by a pumping device, care must be taken to discontinue pumping action before the container runs dry or air embolism may result.

These solutions are intended for intravenous administration using sterile equipment. It is recommended that intravenous administration apparatus be replaced at least once every 24 hours.

Instructions for the Administration of Gentamicin Sulfate in 0.9% Sodium Chloride Injection.

This product is intended for use only as an IV secondary medication unit.

Use aseptic technique when removing contents from these units.

Do not add other drugs to Gentamicin Sulfate in 0.9% Sodium Chloride Injection.

All injections in VIAFLEX PLUS plastic containers are intended for intravenous administration using sterile equipment.

HOW SUPPLIED

Gentamicin Sulfate in 0.9% Sodium Chloride Injection in VIAFLEX PLUS plastic container is available in the following sizes and concentrations.

Gentamicin 60 mg | 50 mL unit: | 2B0851, NDC 0338-0507-41
Gentamicin 80 mg | 50 mL unit: 100 mL unit: | 2B0852, NDC 0338-0509-41 2B0862, NDC 0338-0503-48
Gentamicin 100 mg | 50 mL unit: 100 mL unit: | 2B0853, NDC 0338-0511-41 2B0863, NDC 0338-0505-48
Gentamicin 120 mg | 100 mL unit: | 2B0864, NDC 0338-0507-48

Do not remove unit from overwrap until ready for use. The overwrap is a moisture barrier. The inner bag maintains the sterility of the product. After removing overwrap, check for minute leaks by squeezing inner bag firmly. If leaks are found, discard solution as sterility may be impaired.

Exposure of pharmaceutical products to heat should be minimized. Avoid excessive heat. It is recommended the product be stored at room temperature (25°C); brief exposure up to 40°C does not adversely affect the product.

DIRECTIONS FOR USE OF VIAFLEX PLUS PLASTIC CONTAINER

Warning: Do not use plastic containers in series connections. Such use could result in air embolism due to residual air being drawn from the primary container before administration of the fluid from the secondary container is completed.

To Open

Tear overwrap down side at slit and remove solution container. Visually inspect the container. If the outlet port protector is damaged, detached, or not present, discard container as solution path sterility may be impaired. Some opacity of the plastic due to moisture absorption during the sterilization process may be observed. This is normal and does not affect the solution quality or safety. The opacity will diminish gradually. Check for leaks. Do not add supplementary medication.

Preparation for Administration

1. Suspend container from eyelet support.
2. Remove protector from outlet port at bottom of container.
3. Attach administration set. Refer to complete directions accompanying set.

Baxter Healthcare Corporation
Deerfield, IL 60015 USA
Printed in USA

07-19-00-5423

Rev. October 2022

Baxter, Viaflex and Viaflex Plus are trademarks of Baxter International Inc.

PACKAGE LABEL - PRINCIPAL DISPLAY PANEL

Container Label - 60 mg / 50 mL

LOT
EXP
NDC 0338-0507-41

Gentamicin Sulfate
in 0.9% Sodium Chloride
Injection

60 mg / 50 mL
(1.2 mg / mL)

Cautions For Intravenous Use Only
Maintain unit in overwrap until ready for
use Do not add supplementary medication
Each 50 mL contains Gentamicin Sulfate
USP (equivalent to 60 mg gentamicin)
450 mg Sodium Chloride USP
pH may have been adjusted with sodium
hydroxide or sulfuric acid
See prescribing information for dosing
Store at room temperature (25°C)
Avoid excessive heat
Sterile Single dose container Rx Only

Baxter Logo
Baxter Healthcare Corporation
Deerfield, IL 60015 USA
Made in USA

2B0851

Container Label - 80 mg / 50 mL

LOT
EXP
NDC 0338-0509-41

Gentamicin Sulfate
in 0.9% Sodium Chloride
Injection

80 mg / 50 mL
(1.6 mg / mL)

Cautions For Intravenous Use Only
Maintain unit in overwrap until ready for
use Do not add supplementary medication
Each 50 mL contains Gentamicin Sulfate
USP (equivalent to 80 mg gentamicin)
450 mg Sodium Chloride USP
pH may havebeen adjusted with sodium
hydroxide or sulfuric acid
See prescribing information for dosing
Store at room temperature(25°C)
Avoid excessive heat
Sterile Single dose container Rx Only

Baxter Logo
Baxter Healthcare Corporation
Deerfield IL 60015 USA
Made in USA

2B0852

Container Label Code - 100 mg / 100 mL

LOT
EXP
NDC 0338-0505-48

Gentamicin Sulfate
in 0.9% Sodium Chloride
Injection

100 mg / 100 mL
(1 mg / mL)

Cautions For Intravenous Use Only
Maintain unit in overwrap until ready
for use Do not add supplementary
medication
Each 100 mL contains Gentamicin
Sulfate USP (equivalent to 100 mg
Gentamicin) 900 mg Sodium Chloride
USP pH may have been adjusted with
sodium hydroxide or sulfuric acid
See prescribing information for dosing
Store at room temperature (25°C)
Avoid excessive heat
Sterile Single Dose Container
Rx Only

Baxter Logo
Baxter Healthcare Corporation
Deerfield IL 60015 USA
Made in USA

2B0863

Container Label Code - 100 mg / 50 mL

LOT
EXP
NDC 0338-0511-41

Gentamicin Sulfate
in 0.9% Sodium Chloride
Injection

100 mg / 50 mL
(2 mg / mL)

Cautions For Intravenous Use Only
Maintain unit in overwrap until ready for
use Do not add supplementary medication
Each 50 mL contains Gentamicin Sulfate
USP (equivalent to 100 mg gentamicin)
450 mg Sodium Chloride USP
pH may have been adjusted with sodium
hydroxide or sulfuric acid
See prescribing information for dosing
Store at room temperature (25°C)
Avoid excessive heat
Sterile Single dose container Rx Only

Baxter Logo
Baxter Healthcare Corporation
Deerfield IL 60015 USA

2B0853

Container Label Code - 80 mg / 100 mL

LOT
EXP
NDC 0338-0503-48

Gentamicin Sulfate
in 0.9% Sodium Chloride
Injection

80 mg / 100 mL
(0.8 mg / mL)

Cautions For Intravenous Use Only
Maintain unit in overwrap until ready
for use Do not add supplementary
medication
Each 100 mL contains Gentamicin
Sulfate USP (equivalent to 80 mg
gentamicin) 900 mg Sodium Chloride
USP pH may have been adjusted with
sodium hydroxide or sulfuric acid
See prescribing information for dosing
Store at room temperature (25°C)
Avoid excessive heat
Sterile Single Dose Container
Rx Only

Baxter Logo
Baxter Healthcare Corporation
Deerfield IL 60015 USA
MADE IN USA

2B0862

Container Label

LOT EXP

NDC 0338-0507-48

Gentamicin Sulfate
in 0.9% Sodium Chloride
Injection

120 mg / 100 mL
(1.2 mg / mL)

CAUTIONS FOR INTRAVENOUS USE ONLY
MAINTAIN UNIT IN OVERWRAP UNTIL READY
FOR USE DO NOT ADD SUPPLEMENTARY
MEDICATION

EACH 100 mL CONTAINS GEN TAMICIN
SULFATE USP (EQUIVALEN T TO 120 mg
GENTAMICIN) 900 mg SODIUM CHLORIDE
USP pH MAY HAVE BEEN ADJUSTED WITH
SODIUM HYDROXIDE OR SULFURIC ACID
SEE PRESCRIBING INFORMATION FOR DOSING
STORE AT ROOM TEMPE RATURE (25°C)
AVOID EXCE SSIVE HEAT
STERILE SINGLE DOSE CONTAINER
Rx ONLY

Baxter Logo
2B0864
BAXTER HEALTHCARE CORPORATION
DEERFIELD IL 60015 USA MADE IN USA